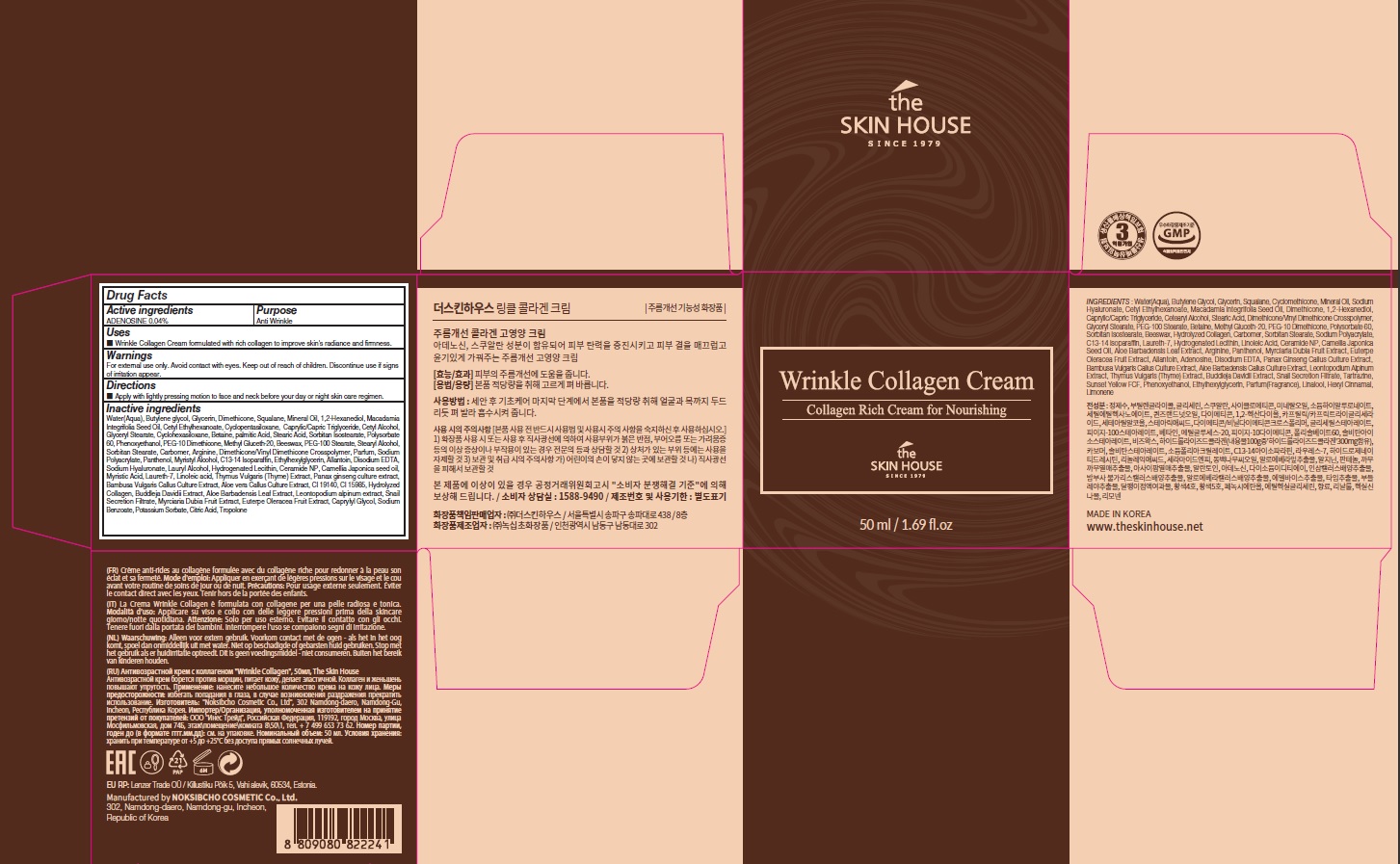 DRUG LABEL: THE SKINHOUSE WRINKLE COLLAGEN
NDC: 73590-0079 | Form: CREAM
Manufacturer: NOKSIBCHO cosmetic Co., Ltd.
Category: otc | Type: HUMAN OTC DRUG LABEL
Date: 20210715

ACTIVE INGREDIENTS: ADENOSINE 0.02 g/50 mL
INACTIVE INGREDIENTS: Water; Butylene Glycol; Glycerin

Drug Facts

ACTIVE INGREDIENT

ADENOSINE 0.04%

INACTIVE INGREDIENTS

Water(Aqua), Butylene glycol, Glycerin, Dimethicone, Squalane, Mineral Oil, 1,2-Hexanediol, Macadamia Integrifolia Seed Oil, Cetyl Ethylhexanoate, Cyclopentasiloxane, Caprylic/Capric Triglyceride, Cetyl Alcohol, Glyceryl Stearate, Cyclohexasiloxane, Betaine, palmitic Acid, Stearic Acid, Sorbitan Isostearate, Polysorbate 60, Phenoxyethanol, PEG-10 Dimethicone, Methyl Gluceth-20, Beeswax, PEG-100 Stearate, Stearyl Alcohol, Sorbitan Stearate, Carbomer, Arginine, Dimethicone/Vinyl Dimethicone Crosspolymer, Parfum, Sodium Polyacrylate, Panthenol, Myristyl Alcohol, C13-14 Isoparaffin, Ethylhexylglycerin, Allantoin, Disodium EDTA, Sodium Hyaluronate, Lauryl Alcohol, Hydrogenated Lecithin, Ceramide NP, Camellia Japonica seed oil, Myristic Acid, Laureth-7, Linoleic acid, Thymus Vulgaris (Thyme) Extract, Panax ginseng culture extract, Bambusa Vulgaris Callus Culture Extract, Aloe vera Callus Culture Extract, CI 19140, CI 15985, Hydrolyzed Collagen, Buddleja Davidii Extract, Aloe Barbadensis Leaf Extract, Leontopodium alpinum extract, Snail Secretion Filtrate, Myrciaria Dubia Fruit Extract, Euterpe Oleracea Fruit Extract, Caprylyl Glycol, Sodium Benzoate, Potassium Sorbate, Citric Acid, Tropolone

PURPOSE

Anti wrinkle

WARNINGS

For external use only.
Avoid contact with eyes.
Keep out of reach of children.
Discontinue use if signs of irritation appear.

KEEP OUT OF REACH OF CHILDREN

Uses

■ Wrinkle Collagen Cream formulated with rich collagen to improve skin's radiance and¬firmness.

Directions

■ Apply with lightly pressing motion to face and neck before your day or night skin care regimen.